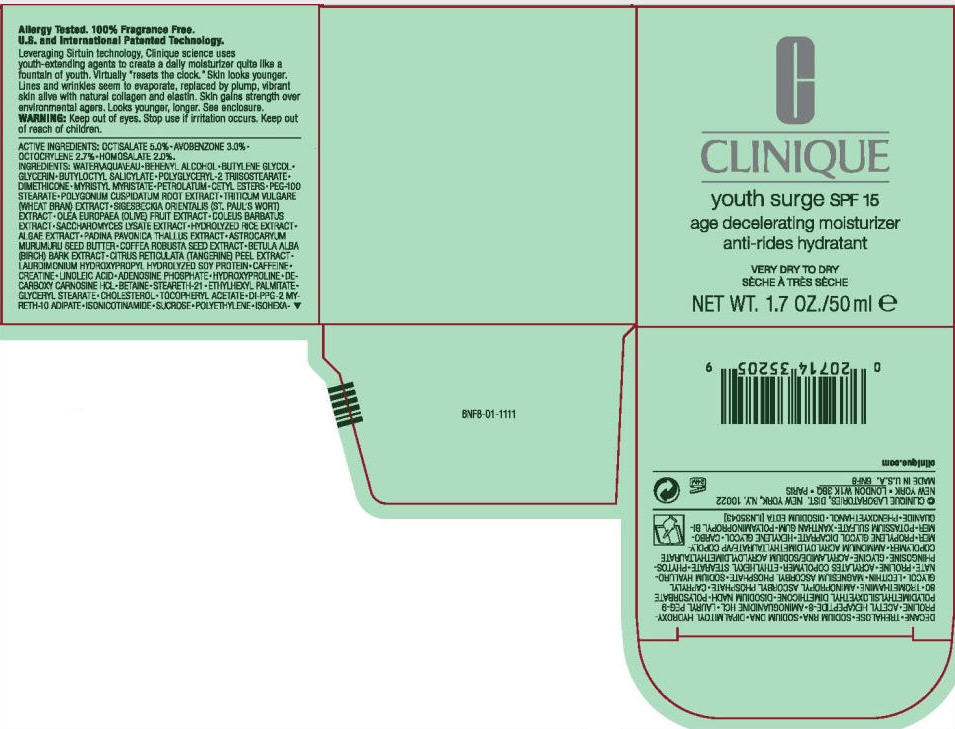 DRUG LABEL: YOUTH SURGE 
NDC: 49527-732 | Form: CREAM
Manufacturer: CLINIQUE  LABORATORIES INC.
Category: otc | Type: HUMAN OTC DRUG LABEL
Date: 20111005

ACTIVE INGREDIENTS: octisalate 5 mL/100 mL; avobenzone 3 mL/100 mL; octocrylene 2.7 mL/100 mL; homosalate 2 mL/100 mL
INACTIVE INGREDIENTS: water; butylene glycol; glycerin; butyloctyl salicylate; dimethicone; docosanol; myristyl myristate; petrolatum; cetyl esters wax; peg-100 stearate; polygonum cuspidatum root; wheat bran; black olive; plectranthus barbatus root; saccharomyces lysate; astrocaryum murumuru seed butter; robusta coffee bean; betula pubescens bark; tangerine peel; caffeine; creatine; linoleic acid; adenosine phosphate; hydroxyproline; betaine; steareth-21; ethylhexyl palmitate; glyceryl monostearate; cholesterol; alpha-tocopherol acetate; sucrose; high density polyethylene; isohexadecane; trehalose; dipalmitoyl hydroxyproline; Pimagedine Hydrochloride; polysorbate 80; tromethamine; caprylyl glycol; magnesium ascorbyl phosphate; hyaluronate sodium; proline; ethylhexyl stearate; glycine; propylene glycol dicaprate; hexylene glycol; potassium sulfate; xanthan gum; edetate disodium; polyaminopropyl biguanide; phenoxyethanol

CLINIQUE
youth surge SPF 15
age decelerating moisturizer

WARNING

WHEN USING

Keep out of eyes.

Stop use if irritation occurs.

Keep out of reach of children.

ACTIVE INGREDIENTS

OCTISALATE 5.0% • AVOBENZONE 3.0% • OCTOCRYLENE 2.7% • HOMOSALATE 2.0%.

INGREDIENTS

WATER • BEHENYL ALCOHOL • BUTYLENE GLYCOL • GLYCERIN • BUTYLOCTYL SALICYLATE • POLYGLYCERYL-2 TRIISOSTEARATE • DIMETHICONE • MYRISTYL MYRISTATE • PETROLATUM • CETYL ESTERS • PEG-100 STEARATE • POLYGONUM CUSPIDATUM ROOT EXTRACT • TRITICUM VULGARE (WHEAT BRAN) EXTRACT • SIGESBECKIA ORIENTALIS (ST. PAUL'S WORT) EXTRACT • OLEA EUROPAEA (OLIVE) FRUIT EXTRACT • COLEUS BARBATUS EXTRACT • SACCHAROMYCES LYSATE EXTRACT • HYDROLYZED RICE EXTRACT • ALGAE EXTRACT • PADINA PAVONICA THALLUS EXTRACT • ASTROCARYUM MURUMURU SEED BUTTER • COFFEA ROBUSTA SEED EXTRACT • BETULA ALBA (BIRCH) BARK EXTRACT • CITRUS RETICULATA (TANGERINE) PEEL EXTRACT • LAURDIMONIUM HYDROXYPROPYL HYDROLYZED SOY PROTEIN • CAFFEINE • CREATINE • LINOLEIC ACID • ADENOSINE PHOSPHATE • HYDROXYPROLINE • DECARBOXY CARNOSINE HCL • BETAINE • STEARETH-21 • ETHYLHEXYL PALMITATE • GLYCERYL STEARATE • CHOLESTEROL • TOCOPHERYL ACETATE • DI-PPG-2 MYRETH-10 ADIPATE • ISONICOTINAMIDE • SUCROSE • POLYETHYLENE • ISOHEXADECANE • TREHALOSE • SODIUM RNA • SODIUM DNA • DIPALMITOYL HYDROXYPROLINE • ACETYL HEXAPEPTIDE-8 • AMINOGUANIDINE HCL • LAURYL PEG-9 POLYDIMETHYLSILOXYETHYL DIMETHICONE • DISODIUM NADH • POLYSORBATE 80 • TROMETHAMINE • AMINOPROPYL ASCORBYL PHOSPHATE • CAPRYLYL GLYCOL • LECITHIN • MAGNESIUM ASCORBYL PHOSPHATE • SODIUM HYALURONATE • PROLINE • ACRYLATES COPOLYMER • ETHYLHEXYL STEARATE • PHYTOSPHINGOSINE • GLYCINE • ACRYLAMIDE/SODIUM ACRYLOYLDIMETHYLTAURATE COPOLYMER • AMMONIUM ACRYLOYLDIMETHYLTAURATE/VP COPOLYMER • PROPYLENE GLYCOL DICAPRATE • HEXYLENE GLYCOL • CARBOMER • POTASSIUM SULFATE • XANTHAN GUM • POLYAMINOPROPYL BIGUANIDE • PHENOXYETHANOL • DISODIUM EDTA [ILN35043]

© CLINIQUE LABORATORIES, DIST. NEW YORK, N.Y. 10022

PRINCIPAL DISPLAY PANEL - 50 ml Carton

C

CLINIQUE

youth surge SPF 15

age decelerating moisturizer

VERY DRY TO DRY

NET WT. 1.7 OZ./50 ml e